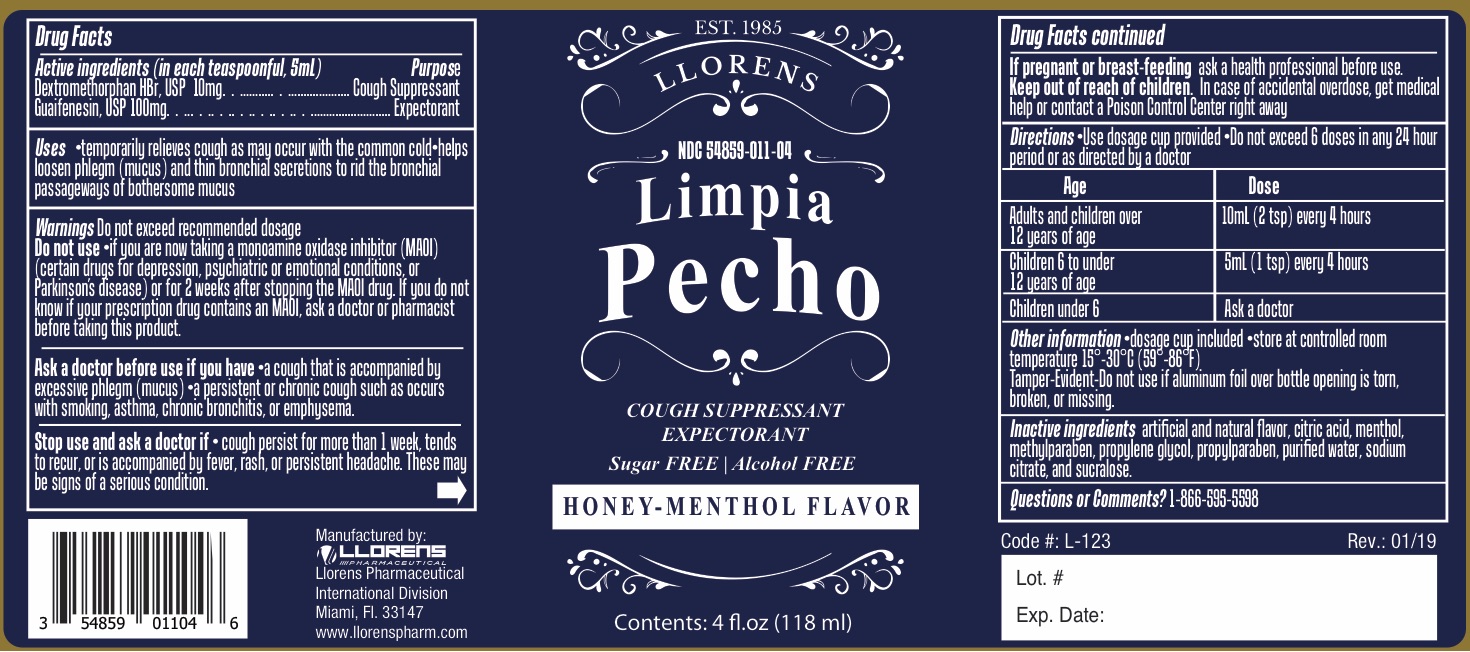 DRUG LABEL: Limpia Pecho
NDC: 54859-011 | Form: LIQUID
Manufacturer: Llorens Pharmaceutical International Division, Inc.
Category: otc | Type: HUMAN OTC DRUG LABEL
Date: 20251231

ACTIVE INGREDIENTS: DEXTROMETHORPHAN HYDROBROMIDE 10 mg/5 mL; GUAIFENESIN 100 mg/5 mL
INACTIVE INGREDIENTS: ANHYDROUS CITRIC ACID; MENTHOL; METHYLPARABEN; PROPYLENE GLYCOL; PROPYLPARABEN; WATER; SODIUM CITRATE; SUCRALOSE

Llorens Limpia Pecho 011

ACTIVE INGREDIENT

In each teaspoonful, 5 mL

Dextromethorphan HBr - 10 mg

Guaifenesin - 100 mg

Purpose

Cough Suppressant

Expectorant

Uses

- temporarily relieves cough as may occur with the common cold
- helps loosen phlegm (mucus) and thin bronchial secretions to rid the bronchial passageways of bothersome mucus

Warnings

Do not exceed recommended dosage

Do not use

- if you are now taking a monoamine oxidase inhibitor (MAOI) (certain drugs for depression, psychiatric or emotional conditions, or Parkinson's disease) or for 2 weeks after stopping the MAOI drug. If you do not know if your prescription drug contains an MAOI, ask a doctor or pharmacist before taking this prduct.

Ask a doctor before use if you have

- a cough that is accompanied by excessive phlegm (mucus)
- a persistent or chronic cough such as occurs with smoking, asthma, chronic bronchitis, or emphysema.

Stop use and ask a dotor if

- cough persist for more than 1 week, tends to recur, or is accompanied by fever, rash, or persistent headache. These may be signs of a serious condition

PREGNANCY

If pregnant or breast-feeding ask a health professional before use.

Keep out of reach of children. In case of accidental overdose, get medical help or contact a Poison Control Center right away.

Directions

- use dosage cup provided
- Do not exceed 6 doses in any 24 hour period or as directed by a doctor

Age | Dose
Adults and children over 12 years of age | 10 mL (2 tsp) every 4 hours
Children 6 to under 12 years of age | 5 mL (1 tsp) every 4 hours
Children under 6 | Ask a doctor

INACTIVE INGREDIENT

Inactive ingredients artificial and natural flavor, citric acid, methol, methylparaben, propylened glycol, propylparaben, purified water, sodium citrate, and sucralose.

Questions or Comments? 1-866-595-5598